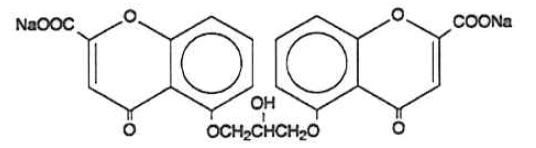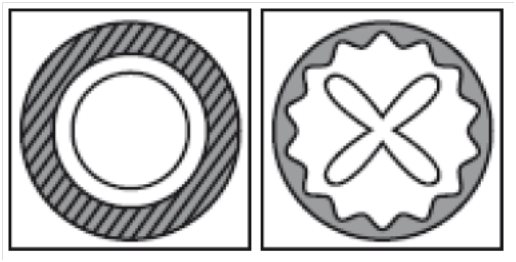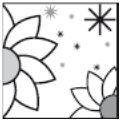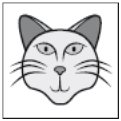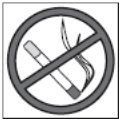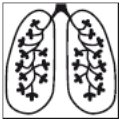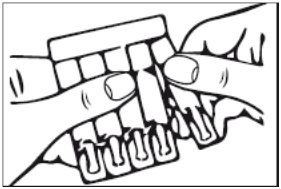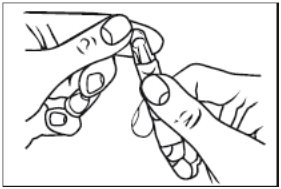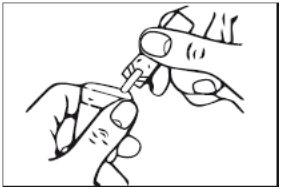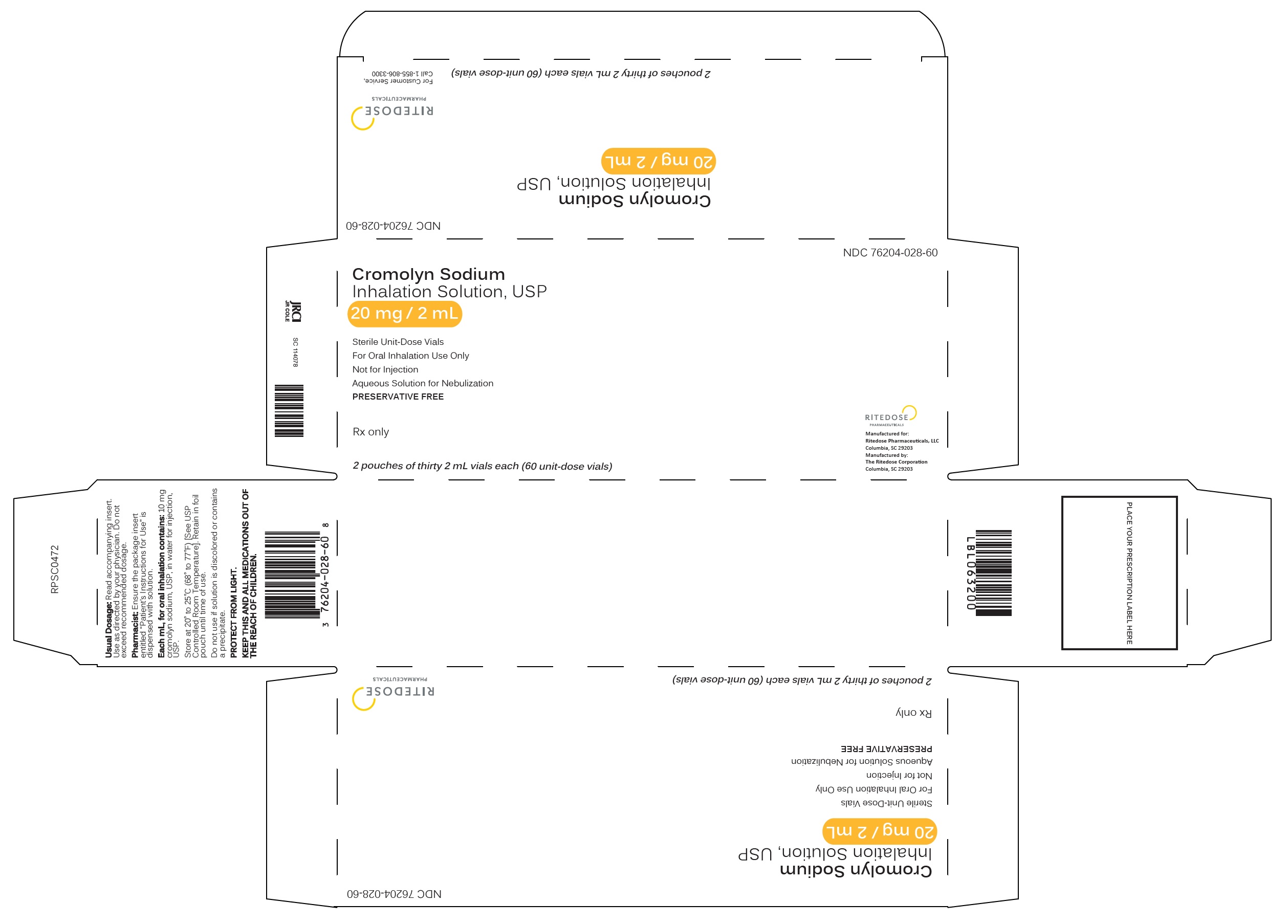 DRUG LABEL: Cromolyn Sodium Inhalation Solution
NDC: 76204-028 | Form: SOLUTION
Manufacturer: Ritedose Pharmaceuticals, LLC
Category: prescription | Type: HUMAN PRESCRIPTION DRUG LABEL
Date: 20251210

ACTIVE INGREDIENTS: CROMOLYN SODIUM 20 mg/2 mL
INACTIVE INGREDIENTS: WATER

Cromolyn Sodium Inhalation Solution, 20 mg/2 mL

For Oral Inhalation Use Only - Not for Injection

Description

The active ingredient of cromolyn sodium inhalation solution USP is cromolyn sodium, USP. It is an inhaled anti-inflammatory agent for the preventive management of asthma. Cromolyn sodium, USP is chemically designated as disodium 5,5'- [(2-hydroxytrimethylene)dioxy] bis [4-oxo-4H-1-benzopyran-2-carboxylate]. The molecular formula is C23H14Na2O11; the molecular weight is 512.34. Cromolyn sodium, USP is a water-soluble, odorless, white, hydrated crystalline powder. It is tasteless at first, but leaves a slightly bitter aftertaste. Cromolyn sodium inhalation solution USP is clear, colorless to pale yellow, sterile and has a target pH of 5.5.

The structural formula is:

Each 2 mL vial for oral inhalation use only contains 20 mg cromolyn sodium, USP in water for injection, USP.

Clinical Pharmacology

In vitro and in vivo animal studies have shown that cromolyn sodium inhibits sensitized mast cell degranulation which occurs after exposure to specific antigens. Cromolyn sodium acts by inhibiting the release of mediators from mast cells. Studies show that cromolyn sodium indirectly blocks calcium ions from entering the mast cell, thereby preventing mediator release.

Cromolyn sodium inhibits both the immediate and non-immediate bronchoconstrictive reactions to inhaled antigen. Cromolyn sodium also attenuates bronchospasm caused by exercise, toluene diisocyanate, aspirin, cold air, sulfur dioxide, and environmental pollutants.

Cromolyn sodium has no intrinsic bronchodilator or antihistamine activity.

After administration by inhalation, approximately 8% of the total cromolyn sodium dose administered is absorbed and rapidly excreted unchanged, approximately equally divided between urine and bile. The remainder of the dose is either exhaled or deposited in the oropharynx, swallowed and excreted via the alimentary tract.

Indications and Usage

Cromolyn sodium inhalation solution USP is a prophylactic agent indicated in the management of patients with bronchial asthma.

In patients whose symptoms are sufficiently frequent to require a continuous program of medication, cromolyn sodium inhalation solution USP is given by inhalation on a regular daily basis (see DOSAGE AND ADMINISTRATION). The effect of cromolyn sodium is usually evident after several weeks of treatment, although some patients show an almost immediate response.

In patients who develop acute bronchoconstriction in response to exposure to exercise, toluene diisocyanate, environmental pollutants, etc., cromolyn sodium should be given shortly before exposure to the precipitating factor (see DOSAGE AND ADMINISTRATION).

Contraindications

Cromolyn sodium inhalation solution is contraindicated in those patients who have shown hypersensitivity to cromolyn sodium.

Warnings

Cromolyn sodium inhalation solution has no role in the treatment of status asthmaticus.

Anaphylactic reactions with cromolyn sodium administration have been reported rarely.

Precautions

General

Occasionally, patients may experience cough and/or bronchospasm following inhalation of cromolyn sodium. At times, patients who develop bronchospasm may not be able to continue cromolyn sodium administration despite prior bronchodilator administration. Rarely, very severe bronchospasm has been encountered.

Symptoms of asthma may recur if cromolyn sodium is reduced below the recommended dosage or discontinued.

Information for Patients

Cromolyn sodium is to be taken as directed by the physician. Because it is preventive medication, it may take up to four weeks before the patient experiences maximum benefit.

Cromolyn sodium should be used in a power-driven nebulizer with an adequate airflow rate equipped with a suitable face mask or mouthpiece.

Drug stability and safety of cromolyn sodium inhalation solution when mixed with other drugs in a nebulizer have not been established.

For additional information, see the accompanying leaflet entitled Living a Full Life with Asthma.

Carcinogenesis, Mutagenesis, and Impairment of Fertility

Long-term studies of cromolyn sodium in mice (12 months intraperitoneal administration at doses up to 150 mg/kg three days per week), hamsters (intraperitoneal administration at doses up to 53 mg/kg three days per week for 15 weeks followed by 17.5 mg/kg three days per week for 37 weeks), and rats (18 months subcutaneous treatment at doses up to 75 mg/kg six days per week) showed no neoplastic effects. These doses correspond to approximately 1.0, 0.3, and 2 times, respectively, the maximum recommended human daily inhalation dose on a mg/m^2 basis.

Cromolyn sodium showed no mutagenic potential in Ames Salmonella/microsome plate assays, mitotic gene conversion in Saccharomyces cerevisiae and in an in vitro cytogenetic study in human peripheral lymphocytes.

No evidence of impaired fertility was shown in laboratory reproduction studies conducted subcutaneously in rats at the highest doses tested, 175 mg/kg/day in males and 100 mg/kg/day in females. These doses are approximately 18 and 10 times, respectively, the maximum recommended adult human daily inhalation dose on a mg/m^2 basis.

Pregnancy: Teratogenic Effects, Pregnancy Category B

Reproduction studies with cromolyn sodium administered subcutaneously to pregnant mice and rats at maximum daily doses of 540 mg/kg and 164 mg/kg, respectively, and intravenously to rabbits at a maximum daily dose of 485 mg/kg produced no evidence of fetal malformations. These doses represent approximately 27, 17, and 98 times, respectively, the maximum recommended adult human daily inhalation dose on a mg/m^2 basis. Adverse fetal effects (increased resorption and decreased fetal weight) were noted only at the very high parenteral doses that produced maternal toxicity. There are, however, no adequate and well-controlled studies in pregnant women.

Because animal reproduction studies are not always predictive of human response, this drug should be used during pregnancy only if clearly needed.

Drug Interaction During Pregnancy

Cromolyn sodium and isoproterenol were studied following subcutaneous injections in pregnant mice. Cromolyn sodium alone in doses up to 540 mg/kg (approximately 27 times the maximum recommended adult human daily inhalation dose on a mg/m^2 basis) did not cause significant increases in resorptions or major malformations. Isoproterenol alone at a dose of 2.7 mg/kg (approximately 7 times the maximum recommended adult human daily inhalation dose on a mg/m^2 basis) increased both resorptions and malformations. The addition of cromolyn sodium (approximately 27 times the maximum recommended adult human daily inhalation dose on a mg/m^2 basis) to isoproterenol (approximately 7 times the maximum recommended adult human daily inhalation dose on a mg/m^2 basis) appears to have increased the incidence of both resorptions and malformations.

Nursing Mothers

It is not known whether this drug is excreted in human milk. Because many drugs are excreted in human milk, caution should be exercised when cromolyn sodium is administered to a nursing woman.

Pediatric Use

Safety and effectiveness in pediatric patients below the age of 2 years have not been established.

Geriatric Use

Clinical studies of cromolyn sodium inhalation solution did not include sufficient numbers of subjects aged 65 and over to determine whether they respond differently from younger subjects. Other reported clinical experience has not identified differences in responses between the elderly and younger patients.

Adverse Reactions

Clinical experience with the use of cromolyn sodium suggests that adverse reactions are rare events. The following adverse reactions have been associated with cromolyn sodium: cough, nasal congestion, nausea, sneezing, and wheezing.

Other reactions have been reported in clinical trials; however, a causal relationship could not be established: drowsiness, nasal itching, nose bleed, nose burning, serum sickness, and stomachache.

In addition, adverse reactions have been reported with cromolyn sodium for inhalation capsules. The most common side effects are associated with inhalation of the powder and include transient cough (1 in 5 patients) and mild wheezing (1 in 25 patients). These effects rarely require treatment or discontinuation of the drug.

Information on the incidence of adverse reactions to cromolyn sodium for inhalation capsules has been derived from U.S. postmarketing surveillance experience. The following adverse reactions attributed to cromolyn sodium, based upon recurrence following readministration, have been reported in less than 1 in 10,000 patients: laryngeal edema, swollen parotid gland, angioedema, bronchospasm, joint swelling and pain, dizziness, dysuria and urinary frequency, nausea, cough, wheezing, headache, nasal congestion, rash, urticaria and lacrimation.

Other adverse reactions have been reported in less than 1 in 100,000 patients, and it is unclear whether these are attributable to the drug: anaphylaxis, nephrosis, periarteritic vasculitis, pericarditis, peripheral neuritis, pulmonary infiltrates with eosinophilia, polymyositis, exfoliative dermatitis, hemoptysis, anemia, myalgia, hoarseness, photodermatitis, and vertigo.

Call your doctor for medical advice about side effects. You may report side effects to Ailex Pharmaceuticals, LLC at 1-888-514-4727 or FDA at 1-800-FDA-1088 or www.fda.gov/medwatch.

Overdosage

There is no clinical syndrome associated with an overdosage of cromolyn sodium. Acute toxicity testing in a wide variety of species has demonstrated that toxicity with cromolyn sodium occurs only with very high exposure levels, regardless of whether administration was parenteral, oral or by inhalation. Parenteral administration in mice, rats, guinea pigs, hamsters, and rabbits demonstrated a median lethal dose of approximately 4000 mg/kg. Intravenous administration in monkeys also indicated a similar pattern of toxicity. The highest dose administered by the oral route in rats and mice was 8000 mg/kg, (approximately 261 and 130 times, respectively, the maximum recommended human daily inhalation dose on a mg/m^2 basis) and at this dose level no deaths occurred. By inhalation, even in long term studies, it proved impossible to achieve toxic dose levels of cromolyn sodium in a range of mammalian species.

Dosage and Administration

For management of bronchial asthma in adults and pediatric patients (two years of age and over), the usual starting dosage is the contents of one vial administered by nebulization four times a day at regular intervals.

Drug stability and safety of cromolyn sodium inhalation solution when mixed with other drugs in a nebulizer have not been established.

Patients with chronic asthma should be advised that the effect of cromolyn sodium inhalation solution therapy is dependent upon its administration at regular intervals, as directed. Cromolyn sodium inhalation solution should be introduced into the patient's therapeutic regimen when the acute episode has been controlled, the airway has been cleared and the patient is able to inhale adequately.

For the prevention of acute bronchospasm which follows exercise or exposure to cold dry air, environmental agents (e.g., animal danders, toluene diisocyanate, pollutants), etc., the usual dose is the contents of one vial administered by nebulization shortly before exposure to the precipitating factor.

It should be emphasized to the patient that the drug is poorly absorbed when swallowed and is not effective by this route of administration.

For additional information, see the accompanying leaflet entitled “Living a Full Life with Asthma”.

Cromolyn Sodium Inhalation Solution Therapy in Relation to Other Treatments for Asthma:

Non-steroidal agents:

Cromolyn sodium inhalation solution should be added to the patient's existing treatment regimen (e.g., bronchodilators). When a clinical response to cromolyn sodium inhalation solution is evident, usually within two to four weeks, and if the asthma is under good control, an attempt may be made to decrease concomitant medication usage gradually.

If concomitant medications are eliminated or required on no more than a prn basis, the frequency of administration of cromolyn sodium inhalation solution may be titrated downward to the lowest level consistent with the desired effect. The usual decrease is from four to three vials per day. It is important that the dosage be reduced gradually to avoid exacerbation of asthma. It is emphasized that in patients whose dosage has been titrated to fewer than four vials per day, an increase in the dose of cromolyn sodium inhalation solution and the introduction of, or increase in, symptomatic medications may be needed if the patient's clinical condition deteriorates.

Corticosteroids:

In patients chronically receiving corticosteroids for the management of bronchial asthma, the dosage should be maintained following the introduction of cromolyn sodium inhalation solution. If the patient improves, an attempt to decrease corticosteroids should be made. Even if the corticosteroid-dependent patient fails to show symptomatic improvement following cromolyn sodium inhalation solution administration, the potential to reduce corticosteroids may nonetheless be present. Thus, gradual tapering of corticosteroid dosage may be attempted. It is important that the dose be reduced slowly, maintaining close supervision of the patient to avoid an exacerbation of asthma.

It should be borne in mind that prolonged corticosteroid therapy frequently causes an impairment in the activity of the hypothalamic-pituitary-adrenal axis and a reduction in the size of the adrenal cortex. A potentially critical degree of impairment or insufficiency may persist asymptomatically for some time even after gradual discontinuation of adrenocortical steroids. Therefore, if a patient is subjected to significant stress, such as a severe asthmatic attack, surgery, trauma or severe illness while being treated or within one year (occasionally up to two years) after corticosteroid treatment has been terminated, consideration should be given to reinstituting corticosteroid therapy. When respiratory function is impaired, as may occur in severe exacerbation of asthma, a temporary increase in the amount of corticosteroids may be required to regain control of the patient's asthma.

It is particularly important that great care be exercised if, for any reason, cromolyn sodium inhalation solution is withdrawn in cases where its use has permitted a reduction in the maintenance dose of corticosteroids. In such cases, continued close supervision of the patient is essential since there may be sudden reappearance of severe manifestations of asthma which will require immediate therapy and possible reintroduction of corticosteroids.

How Supplied

Cromolyn Sodium Inhalation Solution USP Unit-Dose 2 mL Vial is supplied as a colorless to pale yellow solution containing 20 mg cromolyn sodium, USP, in water for injection, USP, with 30 vials per foil pouch in a carton as listed below.

60 vials per carton (NDC 76204-028-60).

Each vial is made from a low density polyethylene (LDPE) resin.

Store at 20° to 25°C (68° to 77°F) [See USP Controlled Room Temperature]. Do not use if solution is discolored or contains a precipitate.

Retain in foil pouch until time of use.

PROTECT FROM LIGHT.

KEEP THIS AND ALL MEDICATIONS OUT OF THE REACH OF CHILDREN.

Manufactured for:
Ritedose Pharmaceuticals, LLC
Columbia, SC 29203 U.S.A.

Manufactured by:

The Ritedose Corporation

Columbia, SC 29203 U.S.A.

Living a Full Life with Asthma Patient Instructions Cromolyn Sodium Inhalation Solution, USP

PATIENT COUNSELING INFORMATION

You or your child may be among the millions of Americans who have asthma. For most patients, asthma need not limit your lifestyle, if you closely follow the asthma management plan your doctor provides you. Your doctor has given you this instruction sheet to help you learn more about asthma and ways to control it.
WHAT IS ASTHMA?
Asthma is a disease that causes patients to have difficulty breathing. Asthma “attacks” occur when the air passages (airways) to the lungs close up, blocking air from passing through. The closing up is caused by two things:

1. The muscles around the airways tighten (constrict) making the airway narrower, and
2. The passage lining swells and produces larger amounts of mucus (a sticky liquid normally found in airways). This swelling is caused by a certain type of inflammation that can build up in the airways of patients with asthma. Inflammation and the airway sensitivity that results from it cause further attacks to occur.

PATIENT COUNSELING INFORMATION

WHAT CAUSES THESE ATTACKS?
Asthma experts know that patients with asthma have attacks because their airways are inflamed and over reactive. Their lungs become super-sensitive to certain irritants or “triggers”, such as cold dry air, pollen, smoke, or cat dander. In the presence of such triggers, someone with asthma may have an attack, and attacks may occur more often. Asthma triggers fall into 6 categories:

1. Substances that cause allergies (pollens, animal dander, molds, house dust, some foods and medicines)
2. Infections that affect breathing (colds, flu)
3. Emotional stress (difficult situations at home, school, or work)
4. Strenuous exercise
5. Irritating gases (chlorine, perfume, tobacco smoke)
6. Sudden changes in temperature or humidity

PATIENT COUNSELING INFORMATION

HOW TO PREVENT ASTHMA ATTACKS
No medicine or procedure will “cure” asthma. The key to asthma relief, therefore, is to prevent attacks and to relieve attack symptoms if they do occur.

A successful prevention plan* will do the following:

1. Keep your activities, including exercise, at normal levels.
2. Keep your lungs functioning normally or at a near-normal level.
3. Prevent symptoms such as coughing or breathlessness that can keep you up at night, or occur in the early morning hours, or after exertion.
4. Prevent asthma attacks from happening.
5. Avoid unpleasant or harmful side effects that may result from using asthma medicine.

The best way to prevent asthma attacks is to avoid the triggers that bother you or your child. Try to identify the specific things that cause problems for you - things such as certain foods, house dust, or animal dander. Avoiding these triggers may be difficult or unpleasant. You may need to find a new home for a family pet or remove a carpet or a favorite stuffed toy. Even though these steps are difficult, they may be necessary in order to help prevent asthma attacks.
If house dust is a trigger, remove dust-collectors such as feather pillows, mattresses, quilts, and carpets from the bedroom. Mattresses and pillows can be covered with allergen-free covers. If a certain food triggers attacks, keep it out of your diet. Irritants in the air can be reduced by air conditioning, electrostatic air filters, or small-pore (HEPA) filters. Be careful of certain medicines. Aspirin and aspirin-like pain relievers, for example, can trigger attacks in some people and should be avoided if they do.
* Adapted from the National Heart, Lung, and Blood Institute: Guidelines for the Diagnosis and Management of Asthma. National Asthma Education Program, Expert Panel Report, 1991

PATIENT COUNSELING INFORMATION

OTHER DO’S AND DON’TS
Anyone with asthma should stick to a healthy, balanced diet,
get lots of rest and moderate exercise, and follow these
do’s and don’ts:

1. Don’t smoke, and don’t stay in the same room with people that do.
2. Avoid fresh paint.
3. Avoid sudden changes of temperature. Don’t go in and out of extremely cool air-conditioned buildings during hot weather.
4. Stay home in extremely cold weather, if possible.
5. Stay away from people with cold or flu.
6. Try to avoid emotionally upsetting situations.
7. Drink lots of liquids.
8. Don’t overdo, but follow a regular exercise plan, including activities that help develop lung capacity.
9. Don’t take any medicine on your own without asking your doctor first.
10. Take all medicines your doctor prescribes, as much and as often as you are told.
11. Avoid taking sleeping pills or sedatives, even if asthma keeps you awake. Prop yourself up with extra pillows until your asthma medicine takes effect.
12. Avoid breathing in insecticides, deodorants, cleaning fluids, chlorine, or other irritating gases.

PATIENT COUNSELING INFORMATION

ASTHMA MEDICINES
Preventive Medicine
Your doctor knows that, besides relieving an attack when it happens, it is also important to prevent attacks from occurring in the first place. Therefore, he or she has prescribed for you cromolyn sodium, a medicine that prevents asthma attacks by making airways less sensitive to asthma triggers. It works by stabilizing cells in the airway lining called mast cells. During an asthma attack, these cells become unstable and give off chemicals called mediators that cause inflammation and asthma attacks. By preventing mediator release, cromolyn sodium works to prevent asthma attacks.
Bronchodilators
When someone is having an asthma attack, he or she needs a medicine called a bronchodilator to open up (dilate) the blocked airways in order to relieve asthma attacks. Your doctor may have already prescribed this medicine for you to use at that time.

PATIENT COUNSELING INFORMATION

HOW WILL CROMOLYN SODIUM WORK FOR YOU?
To get the best possible results, follow your doctor’s instructions carefully when you first take cromolyn sodium.
Your doctor may tell you to take cromolyn sodium 10 to 15 minutes before you exercise or come into contact with a specific trigger, such as a cat. Usually, however, you will be told to take cromolyn sodium on a regular basis, probably starting at four times a day. It is crucial that you take cromolyn sodium, regularly, as often as your doctor recommends, even though you have no asthma symptoms at the time. Cromolyn sodium starts working right away but when you first begin taking it, you may have a lot of inflammation in your airways. Therefore, it may take up to two weeks (or perhaps one month) of regular treatment to bring your asthma under control. Do not stop taking cromolyn sodium or skip any doses without first talking with your doctor.
When you start using cromolyn sodium for the first time, your doctor may ask you to keep a diary showing when you have any symptoms, if and when you have trouble sleeping, how often you wheeze or cough, and other notes to help determine how effective cromolyn sodium will be to help you prevent asthma attacks. Your doctor may also recommend the use of a peak flow meter daily to help you better assess your progress.
While taking cromolyn sodium on a regular basis, you may need to take a bronchodilator-type medicine to treat occasional symptoms or attacks. While taking cromolyn sodium, you should continue taking your other medications until your doctor advises you otherwise.

PATIENT COUNSELING INFORMATION

HOW TO TAKE CROMOLYN SODIUM
Be sure to follow instructions carefully when you are shown how to take cromolyn sodium inhalation solution.

PATIENT COUNSELING INFORMATION

CARE AND STORAGE
Cromolyn sodium nebulizer solution should be stored at 20° to 25°C (68° to 77°F) [See USP Controlled Room Temperature].
Retain in foil pouch until time of use. PROTECT FROM LIGHT.
Do not use if it contains a precipitate (particles or cloudiness) or becomes discolored.
KEEP THIS AND ALL MEDICATIONS OUT OF THE REACH OF CHILDREN.
NOTE: In case of difficulty consult your doctor or pharmacist

Instructions for the Use of Cromolyn Sodium Inhalation Solution, USP

An aqueous solution for nebulization

NOT FOR INJECTION

For best results, follow these instructions exactly and observe Care and Storage directions.

METHOD OF ADMINISTRATION

Cromolyn sodium inhalation solution is recommended for use in a power driven nebulizer operated at an airflow rate of 6-8 liters per minute and equipped with a suitable face mask. Hand-operated nebulizers are not suitable for the administration of cromolyn sodium inhalation solution. Your doctor will advise on the choice of a suitable nebulizer and how it should be used. Do not use any appliance without consulting your doctor.

Drug stability and safety of cromolyn sodium inhalation solution when mixed with other drugs in a nebulizer have not been established.

DOSAGE

Nebulization should be carried out four times a day at regular intervals, or as directed by your doctor. Use the contents of a fresh vial each time.

INHALATION

Once the nebulizer has been assembled and contains cromolyn sodium inhalation solution, hold the mask close to the patient’s face and switch on the device. The patient should breathe in through the mouth and out through the nose in a normal, relaxed manner. Nebulization should take approximately five to ten minutes.

1. Remove a single unit-dose vial from strip (Figure 1)

Figure 1

2. Open the unit-dose vial by twisting off the tabbed top section (Figure 2).

Figure 2

3. Squeeze the contents of the unit-dose vial into the solution container of your nebulizer (Figure 3). Discard the empty unit-dose vial.

Figure 3